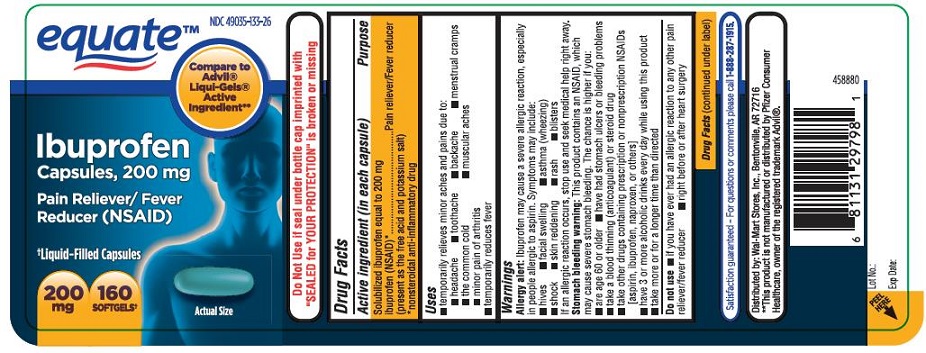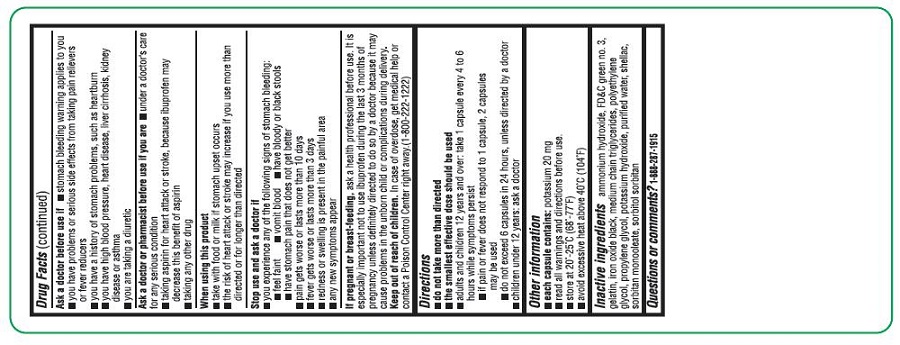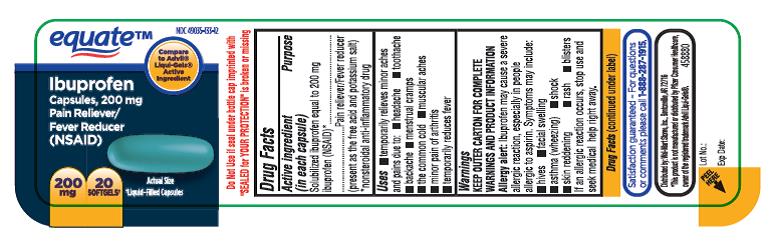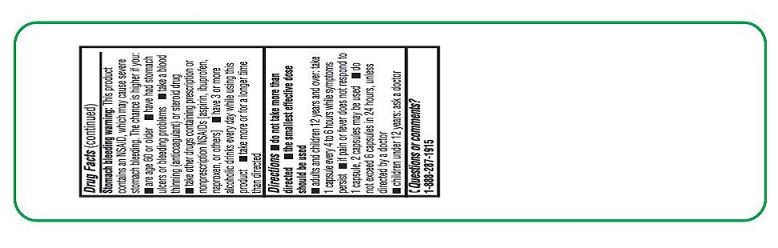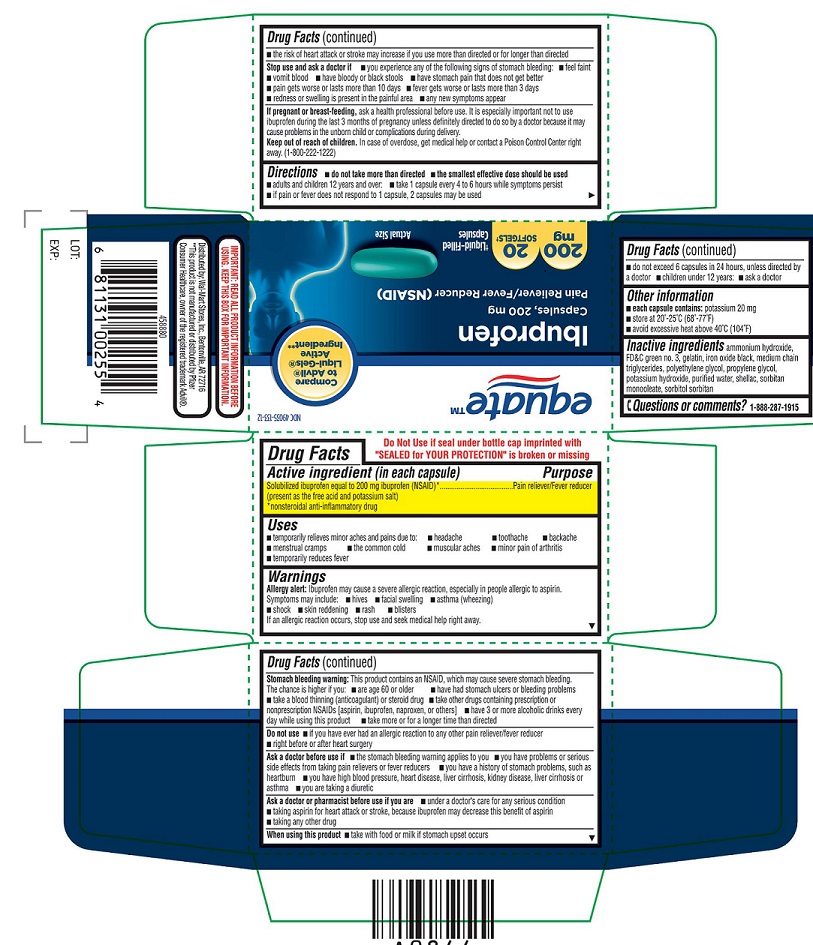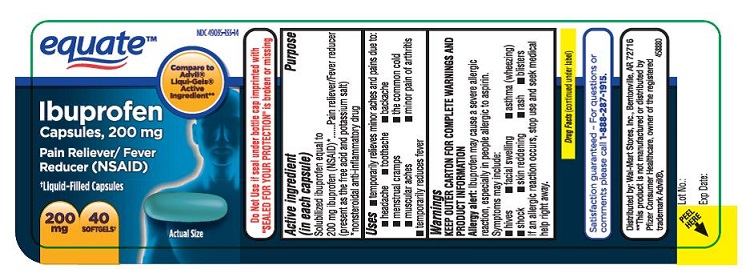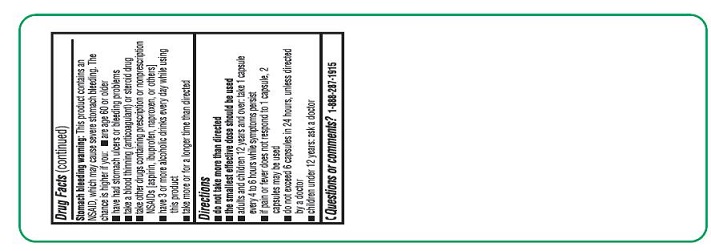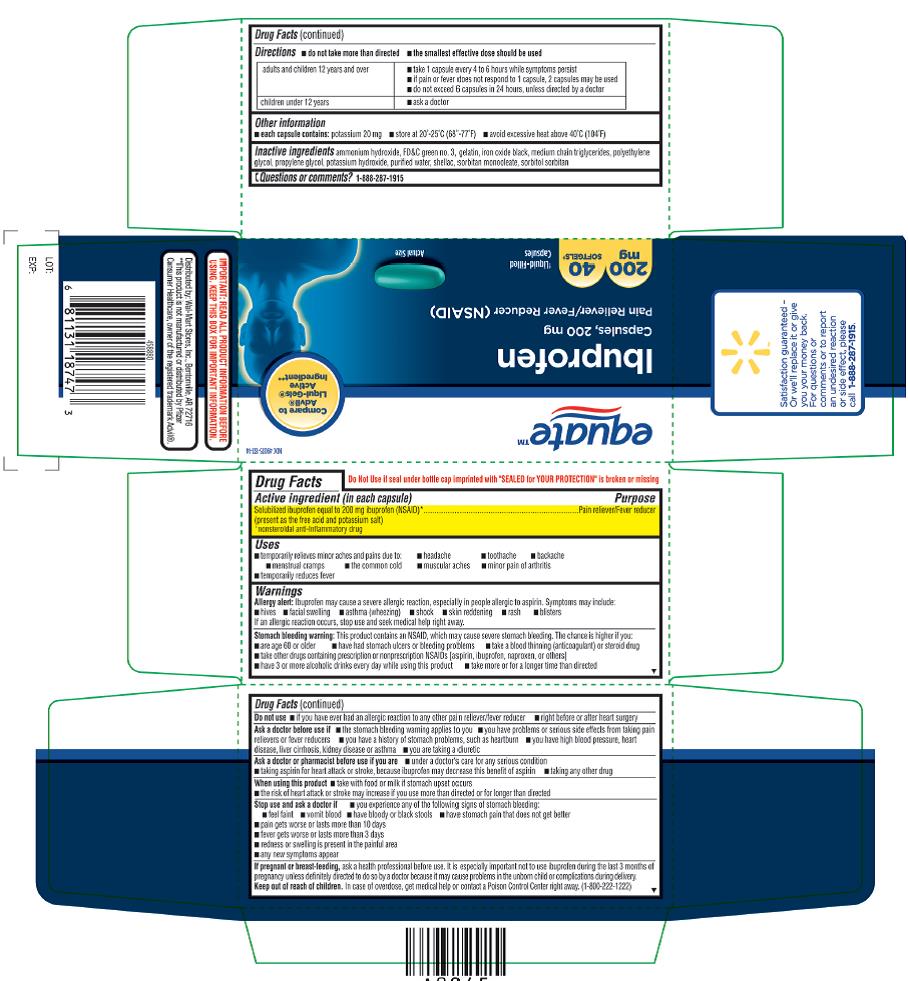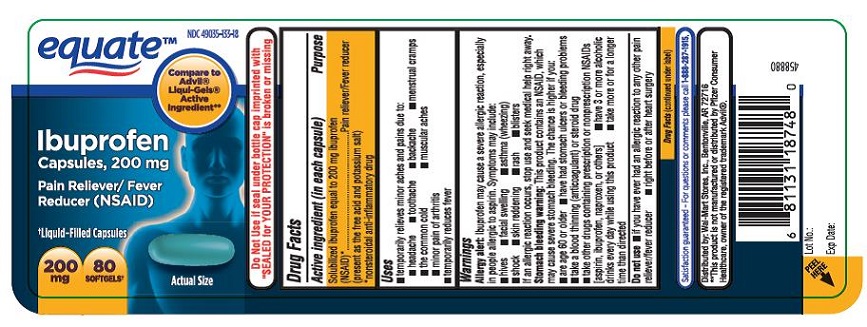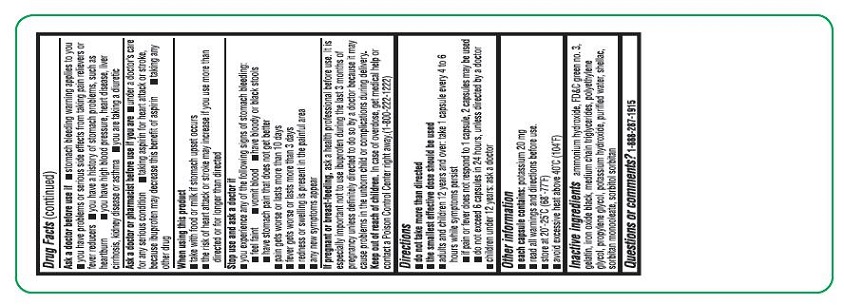 DRUG LABEL: Equate Ibuprofen
NDC: 49035-133 | Form: CAPSULE, LIQUID FILLED
Manufacturer: Walmart stores Inc
Category: otc | Type: Human OTC Drug Label
Date: 20140701

ACTIVE INGREDIENTS: IBUPROFEN 200 mg/1 1
INACTIVE INGREDIENTS: AMMONIA; FD&C GREEN NO. 3; GELATIN; FERROSOFERRIC OXIDE; MEDIUM-CHAIN TRIGLYCERIDES; POLYETHYLENE GLYCOL 400; PROPYLENE GLYCOL; POTASSIUM HYDROXIDE; WATER; SHELLAC; SORBITAN MONOOLEATE; SORBITOL; SORBITAN

ACTIVE INGREDIENT(S)

Solubilized ibuprofen equal to 200 mg ibuprofen (NSAID)*
(Present as the free acid and potassium salt)

*nonsteroidal anti-inflammatory drug

PURPOSE

Pain reliever/Fever reducer

USE(S)

- temporarily relieves minor aches and pains due to:
- headache
- toothache
- backache
- menstrual cramps
- the common cold
- muscular aches
- minor pain of arthritis
- temporarily reduces fever

WARNINGS

Allergy alert:

Ibuprofenmay cause a severe allergic reaction, especially in people allergic to aspirin.Symptoms may include:

- hives
- facial swelling
- asthma (wheezing)
- shock
- skin reddening
- rash
- blisters

If anallergic reaction occurs, stop use and seek medical help right away.

Stomach bleeding warning:

Thisproduct contains an NSAID, which may cause severe stomach bleeding. The chanceis higher if you

- are age 60 or older
- have had stomach ulcers or bleeding problems
- take a blood thinning (anticoagulant) or steroid drug
- take other drugs containing prescription or nonprescription NSAIDs [aspirin, ibuprofen, naproxen, or others]
- have 3 or more alcoholic drinks every day while using this product
- take more or for a longer time than directed

DO NOT USE

- if you have ever had an allergic reaction to any other pain reliever/fever reducer
- right before or after heart surgery

ASK A DOCTOR BEFORE USE IF

- the stomach bleeding warning applies to you
- you have problems or serious side effects from taking pain relievers or fever reducers
- you have a history of stomach problems, such as heartburn
- you have high blood pressure, heart disease, liver cirrhosis, kidney disease, or asthma
- you are taking a diuretic

ASK A DOCTOR OR PHARMACIST BEFORE USE IF

- under a doctor's care for any serious condition
- taking aspirin for heart attack or stroke, because ibuprofen may decrease this benefit of aspirin
- taking any other drug

WHEN USING THIS PRODUCT

- take with food or milk if stomach upset occurs
- the risk of heart attack or stroke may increase if you use more than directed or for longer than directed

STOP USE AND ASK DOCTOR IF

- you experience any of the following signs of stomach bleeding:
- feel faint
- vomit blood
- have bloody or black stools
- have stomach pain that does not get better
- pain gets worse or lasts more than 10 days
- fever gets worse or lasts more than 3 days
- redness or swelling is present in the painful area
- any new symptoms appear

OTHER REQUIRED WARNINGS

- each capsule contains: potassium 20 mg
- read all warnings and directions before use. Keep carton.
- store at 20-25°C (68-77°F)
- avoid excessive heat above 40°C (104°F)

PREGNANCY/BREASTFEEDING

Ask a health professional before use. It is especiallyimportant not to use ibuprofen during the last 3 months of pregnancy unlessdefinitely directed to do so by a doctor because it may cause problems in theunborn child or complications during delivery.

KEEP OUT OF REACH OF CHILDREN

In case of overdose, get medical help or contact a Poison Control Center right away. (1-800-222-1222)

DIRECTIONS

- do not take more than directed
- the smallest effective dose should be used
- adults and children 12 years and over: take 1 capsule every 4 to 6 hours while symptoms persist
- if pain or fever does not respond to 1 capsule, 2 capsules may be used
- do not exceed 6 capsules in 24 hours, unless directed by a doctor
- children under 12 years: ask a doctor

INACTIVE INGREDIENT(S)

Ammonium hydroxide, FD&C green no.3, Gelatin, Iron oxide black (ferrosoferric oxide), Medium chain triglycerides, Polyethylene glycol, Propylene glycol, Potassium hydroxide, Purified water, Shellac, Sorbitol, Sorbitan monooleate

PRINCIPAL DISPLAY PANEL

NDC 49035-133-12

equateTM

Ibuprofen

Capsules, 200mg

Pain Reliever/ Fever Reducer

(NSAID)

200mg, 20 SOFTGELS

Liquid-Filled Capsules

NDC 49035-133-14

equateTM

Ibuprofen

Capsules, 200mg

Pain Reliever/ Fever

Reducer (NSAID)

Liquid-Filled Capsules

200mg, 40 SOFTGELS

NDC 49035-133-18

equateTM

Ibuprofen

Capsules, 200mg

Pain Reliever/ Fever

Reducer (NSAID)

Liquid-Filled Capsules

200mg, 80 SOFTGELS

NDC 49035-133-26

equateTM

Ibuprofen

Capsules, 200mg

Pain Reliever/ Fever

Reducer (NSAID)

Liquid-Filled Capsules

200mg, 160 SOFTGELS